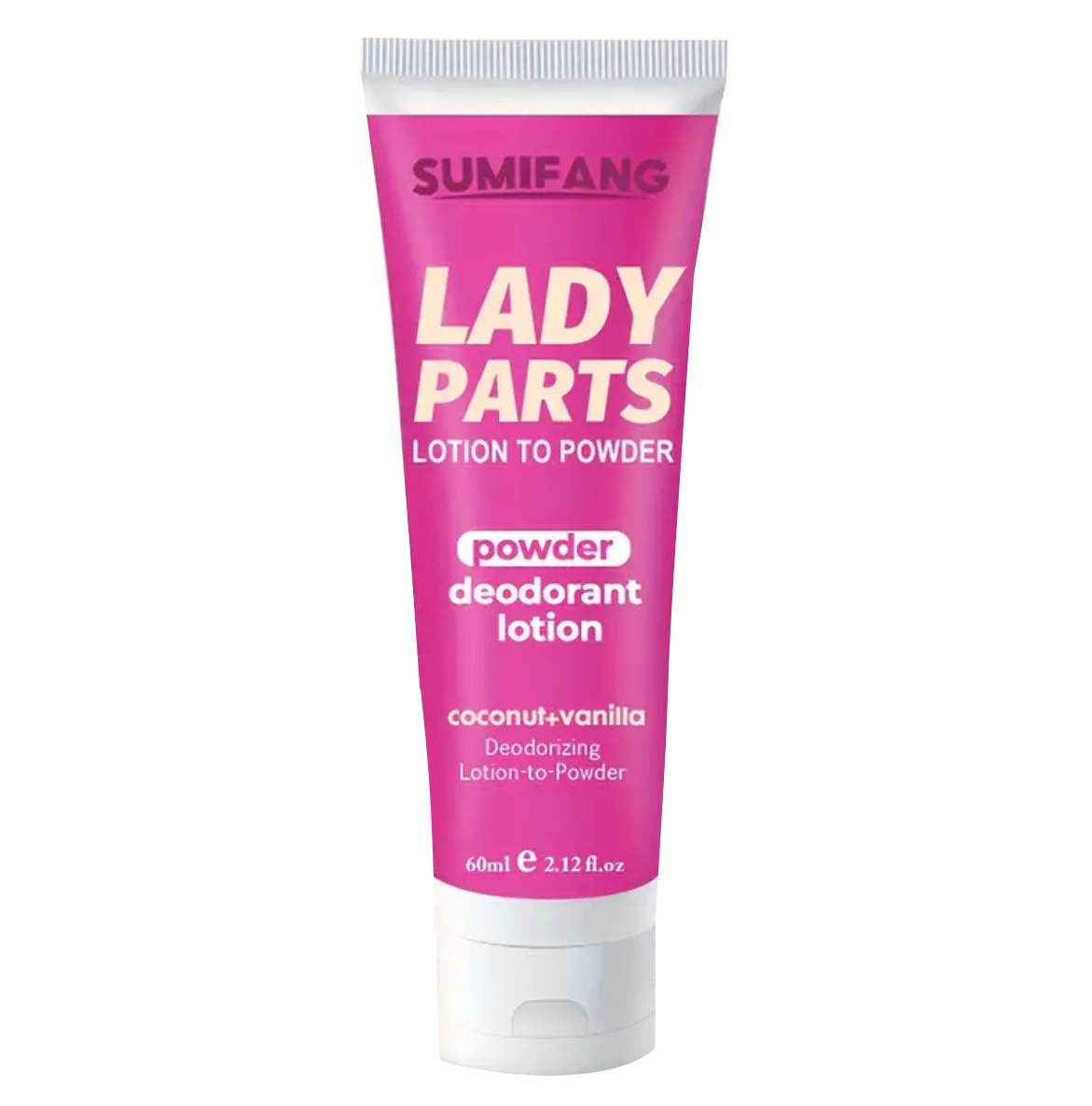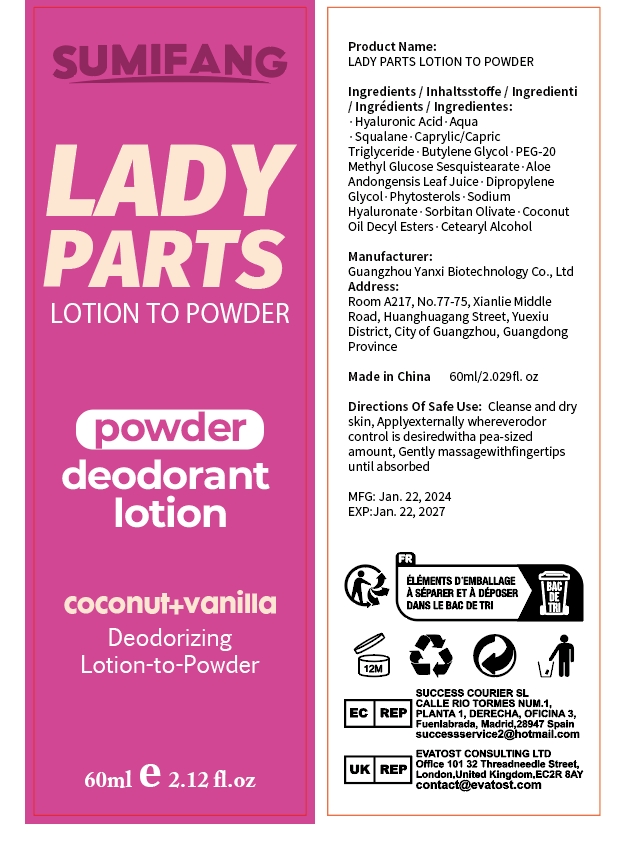 DRUG LABEL: Lady PartsLotion
NDC: 84025-094 | Form: LOTION
Manufacturer: Guangzhou Yanxi Biotechnology Co.. Ltd
Category: otc | Type: HUMAN OTC DRUG LABEL
Date: 20240729

ACTIVE INGREDIENTS: HYALURONIC ACID 5 mg/60 mL; SQUALANE 3 mg/60 mL
INACTIVE INGREDIENTS: WATER

WARNINGS

keep out of children

INACTIVE INGREDIENT

Aqua

INDICATIONS AND USAGE

For daily skin care

DOSAGE AND ADMINISTRATION

Use as a daily skin lotion

Keep out of children

PURPOSE

For daily moisturizing and care of the skin